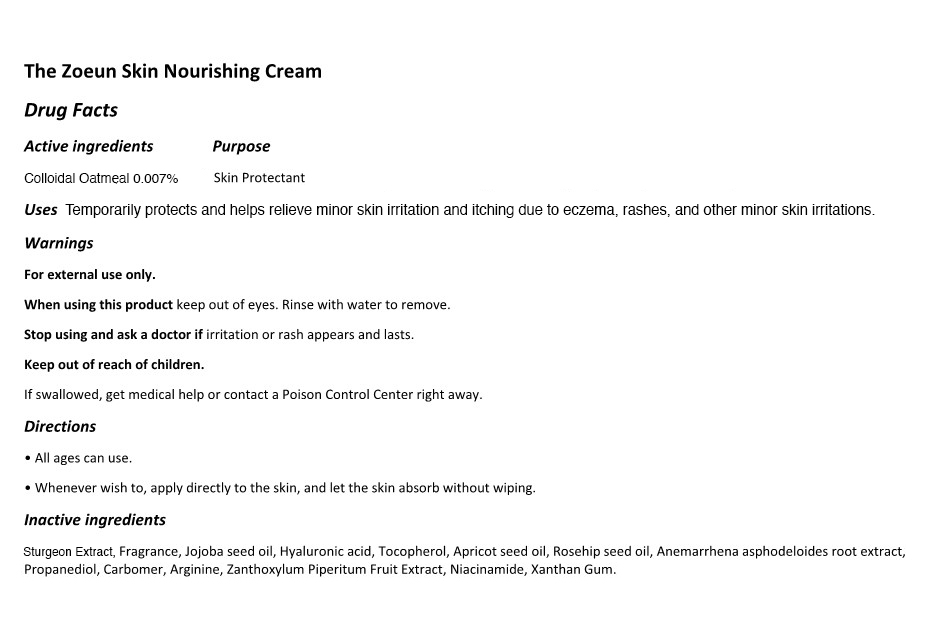 DRUG LABEL: The Zoeun Skin Nourishing Cream
NDC: 83636-118 | Form: CREAM
Manufacturer: Sturgeonbio Co.,Ltd.
Category: otc | Type: HUMAN OTC DRUG LABEL
Date: 20251001

ACTIVE INGREDIENTS: OATMEAL 0.007 g/100 mL
INACTIVE INGREDIENTS: 1,2-HEXANEDIOL; HYALURONATE SODIUM; JOJOBA OIL; XANTHAN GUM; ACETYL ARGININE; FRAGRANCE 13576; APRICOT KERNEL OIL; ZANTHOXYLUM PIPERITUM FRUIT PULP; PROPANEDIOL; ROSA CANINA SEED; NIACINAMIDE; FISH OIL; ANEMARRHENA ASPHODELOIDES ROOT; STURGEON, UNSPECIFIED; TOCOPHEROL; CARBOXYPOLYMETHYLENE; WATER; BUTYLENE GLYCOL

118 The Zoeun Skin Nourishing Cream

Active Ingredients

Colloidal Oatmeal 0.007%

Purpose

Skin protectant

Uses

Temporarily protects and helps relieve minor skin irritation and itching due to eczema, rashes, insect bites, and other minor skin irritations. Helps protect and soothe dry skin.

Warnings

- Keep out of reach of children.
- If swallowed, get medical help or contact a Poison Control Center right away.

Warnings

Stop using and ask a doctor if irritation or rash appears and lasts.

Warnings

- When using this product keep out of eyes.
- Rinse with water to remove.

Warnings

For external use only.

Directions

- All ages can use.
- Whenever wish to, apply directly to the skin, and let the skin absorb without wiping.

Inactive Ingredients

Sturgeon Extract, Fragrance, Jojoba seed oil, Hyaluronic acid, Tocopherol, Apricot seed oil, Rosehip seed oil, Anemarrhena asphodeloides root extract, Propanediol, Carbomer, Arginine, Zanthoxylum Piperitum Fruit Extract, Niacinamide, Xanthan Gum